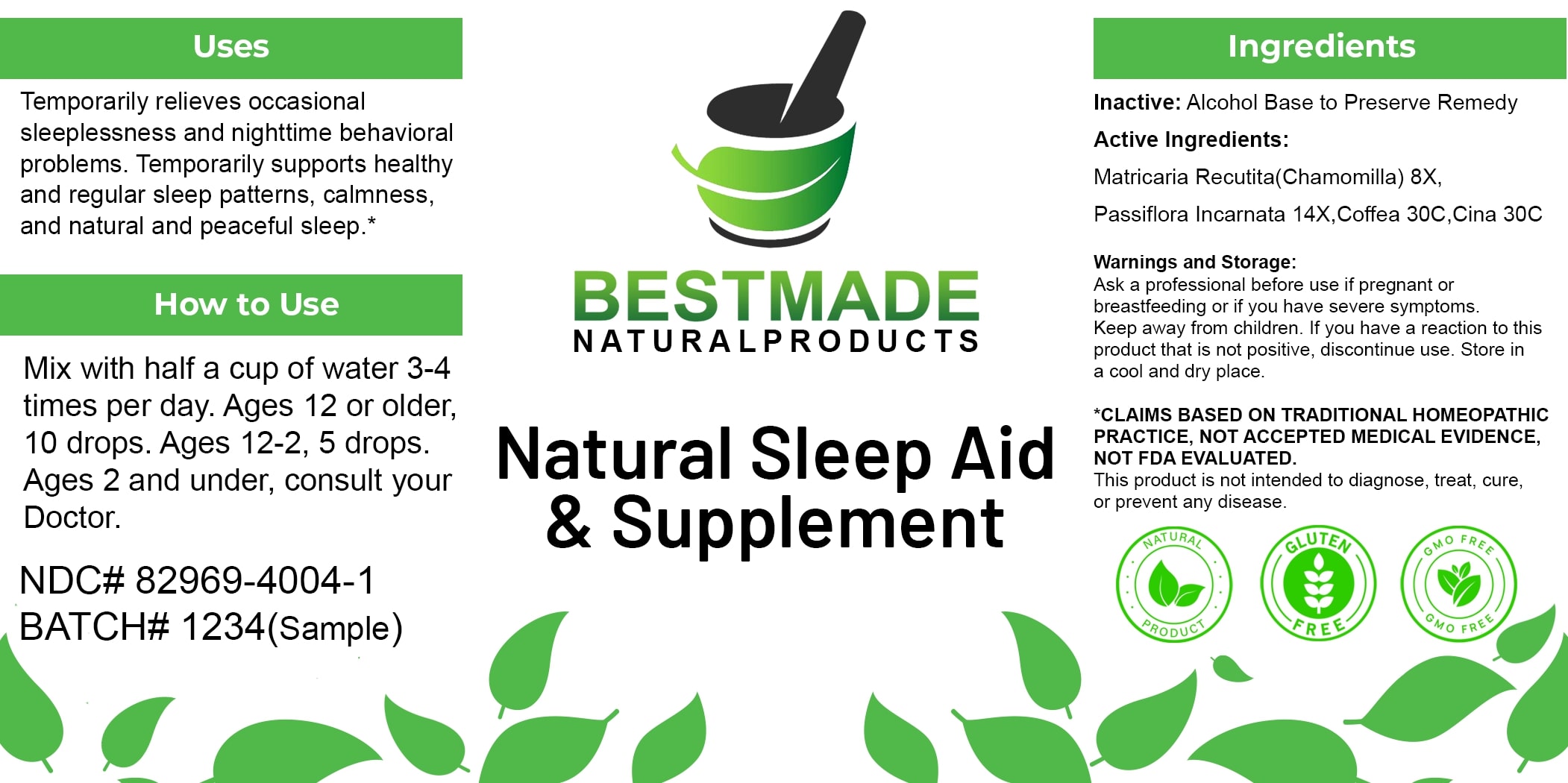 DRUG LABEL: Bestmade Natural Products Natural Sleep Aid and Supplement
NDC: 82969-4004 | Form: LIQUID
Manufacturer: Bestmade Natural Products
Category: homeopathic | Type: HUMAN OTC DRUG LABEL
Date: 20250307

ACTIVE INGREDIENTS: ARTEMISIA CINA PRE-FLOWERING TOP 30 [hp_C]/30 [hp_C]; PASSIFLORA INCARNATA FLOWERING TOP 14 [hp_X]/30 [hp_C]; ARABICA COFFEE BEAN 30 [hp_C]/30 [hp_C]; MATRICARIA CHAMOMILLA 8 [hp_X]/30 [hp_C]
INACTIVE INGREDIENTS: ALCOHOL 30 [hp_C]/30 [hp_C]

Natural Sleep Aid & Supplement

DOSAGE AND ADMINISTRATION

How to Use

Mix with half a cup of water 3-4 times per day. Ages 12 or older, 10 drops. Ages 12-2, 5 drops. Ages 2 and under, consult your Doctor.

INACTIVE INGREDIENT

Ingredients

Inactive: Alcohol Base to Preserve Remedy

ACTIVE INGREDIENT

Active Ingredients: Matricaria Recutita (Chamomilla) 8X, Passiflora Incarnata 14X, Coffea 30C, Cina 30C

Uses

Temporarily relieves occasional sleeplessness and nighttime behavioral problems. Temporarily supports healthy and regular sleep patterns, calmness, and natural and peaceful sleep.*

*CLAIMS BASED ON TRADITIONAL HOMEOPATHIC PRACTICE, NOT ACCEPTED MEDICAL EVIDENCE, NOT FDA EVALUATED.

This product is not intended to diagnose, treat, cure, or prevent any disease.

Uses

Temporarily relieves occasional sleeplessness and nighttime behavioral problems. Temporarily supports healthy and regular sleep patterns, calmness, and natural and peaceful sleep.*

*CLAIMS BASED ON TRADITIONAL HOMEOPATHIC PRACTICE, NOT ACCEPTED MEDICAL EVIDENCE, NOT FDA EVALUATED.

This product is not intended to diagnose, treat, cure, or prevent any disease.

KEEP OUT OF REACH OF CHILDREN

Warnings and Storage:

Ask a professional before use if pregnant or breastfeeding or if you have severe symptoms. Keep away from children. If you have a reaction to this product that is not positive, discontinue use. Store in a cool and dry place.

Warnings and Storage:

Ask a professional before use if pregnant or breastfeeding or if you have severe symptoms. Keep away from children. If you have a reaction to this product that is not positive, discontinue use. Store in a cool and dry place.

*CLAIMS BASED ON TRADITIONAL HOMEOPATHIC PRACTICE, NOT ACCEPTED MEDICAL EVIDENCE, NOT FDA EVALUATED.

This product is not intended to diagnose, treat, cure, or prevent any disease.

Entire package label